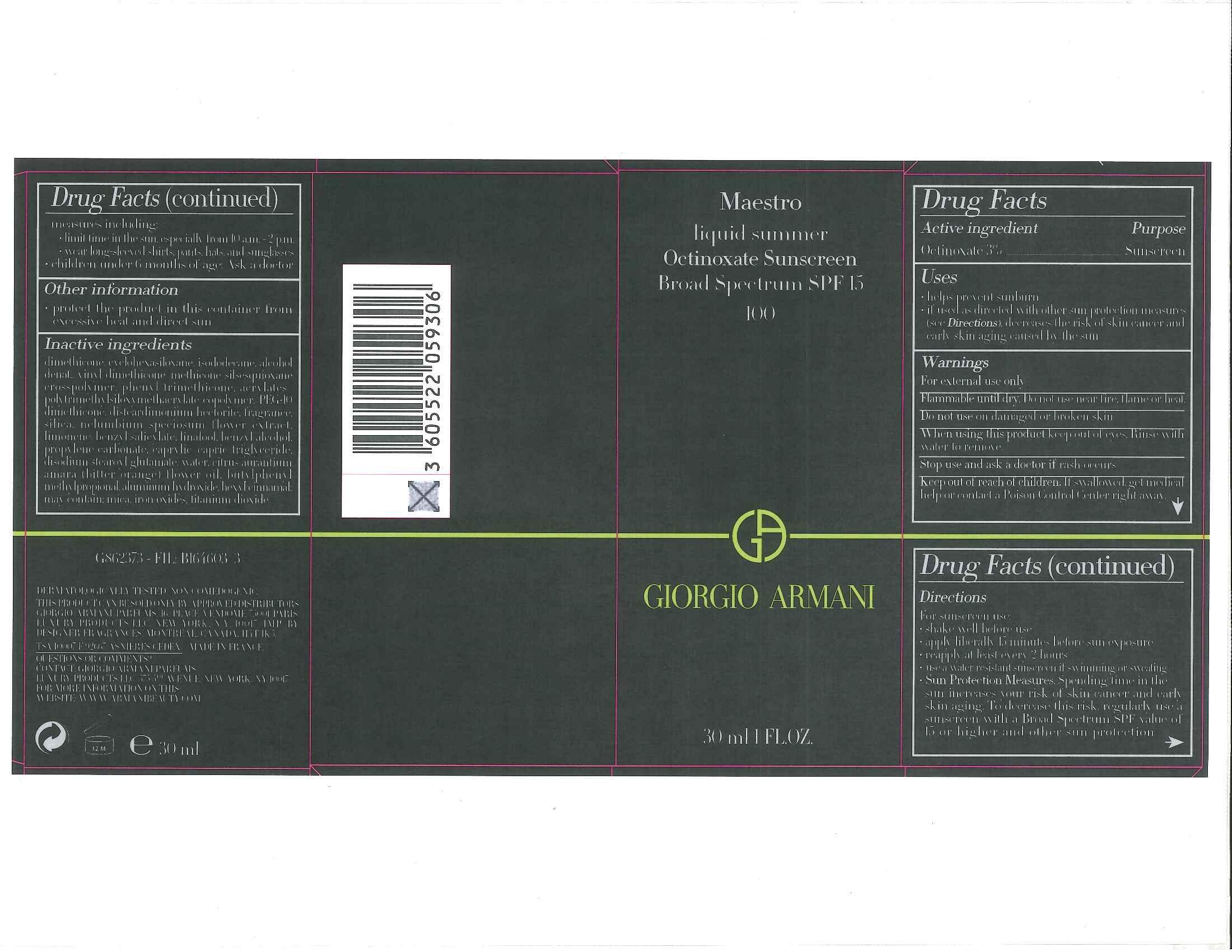 DRUG LABEL: Giorgio Armani Maestro LiquidSummer Broad Spectrum SPF 15 Sunscreen
NDC: 51150-931 | Form: LIQUID
Manufacturer: SICOS ET CIE
Category: otc | Type: HUMAN OTC DRUG LABEL
Date: 20240624

ACTIVE INGREDIENTS: OCTINOXATE 30 mg/1 mL
INACTIVE INGREDIENTS: DIMETHICONE; CYCLOMETHICONE 6; ISODODECANE; ALCOHOL; VINYL DIMETHICONE/METHICONE SILSESQUIOXANE CROSSPOLYMER; PHENYL TRIMETHICONE; PEG-10 DIMETHICONE (600 CST); DISTEARDIMONIUM HECTORITE; SILICON DIOXIDE; LIMONENE, (+)-; BENZYL SALICYLATE; LINALOOL, (+/-)-; BENZYL ALCOHOL; PROPYLENE CARBONATE; MEDIUM-CHAIN TRIGLYCERIDES; DISODIUM STEAROYL GLUTAMATE; WATER; CITRUS AURANTIUM FLOWER OIL; BUTYLPHENYL METHYLPROPIONAL; ALUMINUM HYDROXIDE; .ALPHA.-HEXYLCINNAMALDEHYDE; MICA; FERRIC OXIDE RED; TITANIUM DIOXIDE

Drug Facts

Active ingredient

Octinoxate 3%

Purpose

Sunscreen

Uses

- helps prevent sunburn
- if used as directed with other sun protection measures (see Directions), decreases the risk of skin cancer and early skin aging caused by the sun

Warnings

For external use only

Flammable until dry.

Do not use near fire, flame or heat.

Do not use

on damaged or broken skin

When using this product

keep out of eyes. Rinse with water to remove.

Stop use and ask a doctor if

rash occurs

Keep out of reach of children.

If swallowed, get medical help or contact a Poison Control Center right away.

Directions

For sunscreen use:

● shake well before use

● apply liberally 15 minutes before sun exposure

● reapply at least every 2 hours

● use a water resistant sunscreen if swimming or sweating

● Sun Protection Measures. Spending time in the sun increases your risk of skin cancer and early skin aging. To decrease this risk, regularly use a sunscreen with a Broad Spectrum SPF value of 15 or higher and other sun protection measures including:

● limit time in the sun, especially from 10 a.m. – 2 p.m.

● wear long-sleeved shirts, pants, hats, and sunglasses

● children under 6 months of age: Ask a doctor

Other information

protect the product in this container from excessive heat and direct sun

Inactive ingredients

dimethicone, cyclohexasiloxane, isododecane, alcohol denat., vinyl dimethicone/methicone silsesquioxane crosspolymer, phenyl trimethicone, acrylates/polytrimethylsiloxymethacrylate copolymer, PEG-10 dimethicone, disteardimonium hectorite, fragrance, silica, nelumbium speciosum flower extract, limonene, benzyl salicylate, linalool, benzyl alcohol, propylene carbonate, caprylic/capric triglyceride, disodium stearoyl glutamate, water, citrus aurantium amara (bitter orange) flower oil, butylphenyl methylpropional, aluminum hydroxide, hexyl cinnamal; mayt contain: mica, iron oxides, titanium dioxide